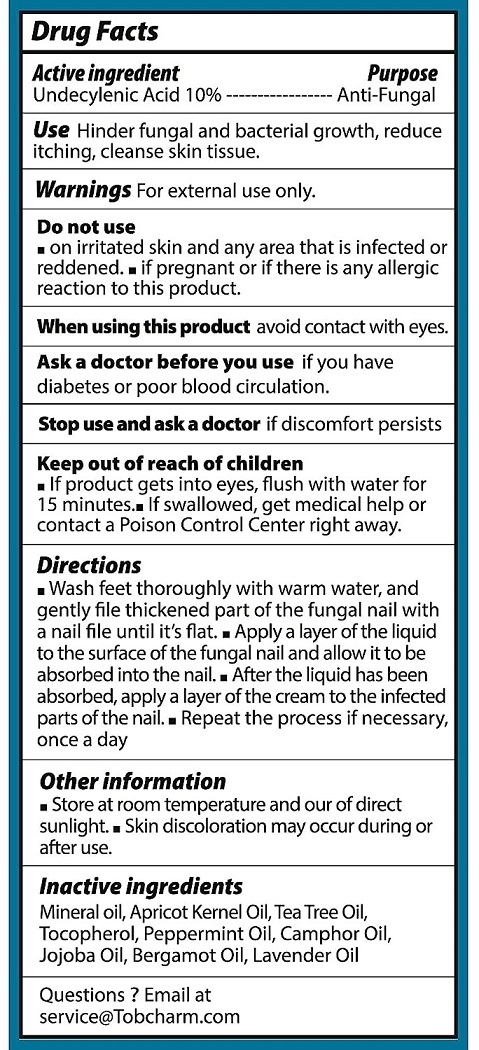 DRUG LABEL: Tobcharm
NDC: 83462-002 | Form: LIQUID
Manufacturer: EUbizrival LLC
Category: otc | Type: HUMAN OTC DRUG LABEL
Date: 20230906

ACTIVE INGREDIENTS: UNDECYLENIC ACID 10 g/100 mL
INACTIVE INGREDIENTS: MINERAL OIL; APRICOT KERNEL OIL; TEA TREE OIL; TOCOPHEROL; PEPPERMINT OIL; CAMPHOR OIL; JOJOBA OIL; BERGAMOT OIL; LAVENDER OIL

Active ingredients

Undecylenic Acid 10%

Purpose

Anti-Fungal

Uses

Hinder fungal and bacterial growth, reduce itching, cleanse skin tissue.

Warnings

For external use only

Do not use

- on irritated skin and any area that is infected or reddened
- if pregnant or if there is any allergic reaction to this product.

When using this product

- avoid contact with eyes.

Stop use and ask a doctor if

- if discomfort persists

Keep out of reach of children.

- if product get into eyes, flush with water for 15 minutes
- if swallowed, get medical help or contact a Poison Control Center right away.

Directions

- Wash feet thoroughly with warm water, and gently file thickened part of the fungal nail with a nail file until its flat
- apply layer of the liquid to the surface of the fungal nail and allow it to be absorbed into the nail.
- after the liquid has been absorbed, apply a layer of the cream to the infected parts of the nail
- repeat the process if necessary once a day

Other information

Store at room temperature and our of direact sunlight. Skin discoloration may occur during or after use.

Inactive ingredients

mineral oil, apricot kernel oil, tea tree oil, tocopherol, peppermint oil, camphor oil, jojoba oil, bergamot oil, lavender oil

Questions ? Email at

service@Tobcharm.com